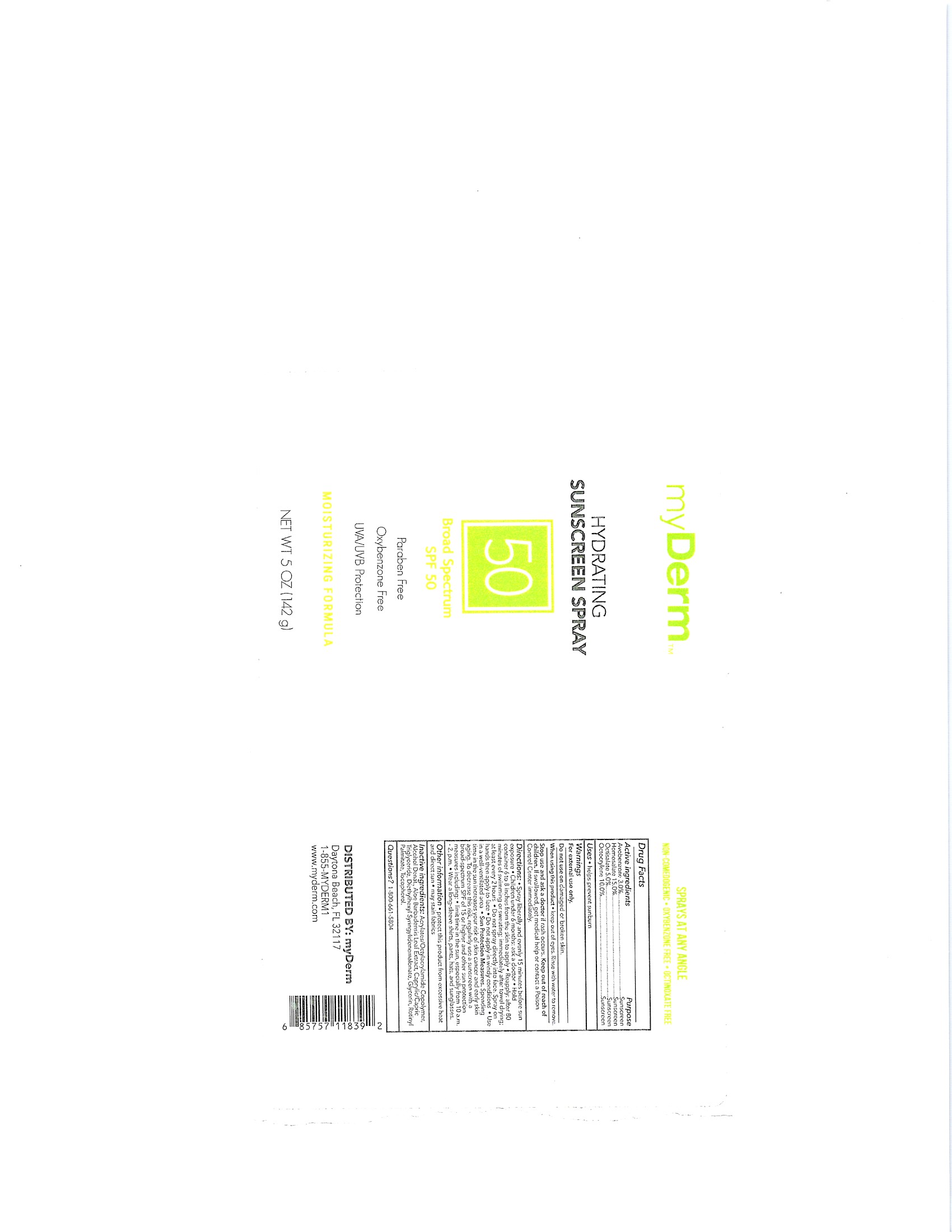 DRUG LABEL: MyDerm Hydrating Sunscreen Broad Spectrum SPF 50
NDC: 72667-075 | Form: SPRAY
Manufacturer: Inspec Solutions
Category: otc | Type: HUMAN OTC DRUG LABEL
Date: 20240624

ACTIVE INGREDIENTS: HOMOSALATE 15 g/100 mL; OCTOCRYLENE 10 g/100 mL; AVOBENZONE 3 g/100 mL; OCTISALATE 5 g/100 mL
INACTIVE INGREDIENTS: GLYCERIN; VITAMIN A PALMITATE; DIETHYLHEXYL SYRINGYLIDENEMALONATE; CAPRYLIC/CAPRIC/LAURIC TRIGLYCERIDE; ALOE VERA LEAF; ACRYLATE/ISOBUTYL METHACRYLATE/N-TERT-OCTYLACRYLAMIDE COPOLYMER (75000 MW); ALCOHOL; .ALPHA.-TOCOPHEROL ACETATE

MyDerm Hydrating Sunscreen Spray Broad Spectrum SPF 50 (IS0002)

Active ingredient

Avobenzone 3.0%

Homosalate 15%

Octisalate 5%

Octocrylene 10%

When using this product:

• keep out of eyes. Rinse with water to remove.

• Keep away from face to avoid breathing it.

• Do not puncture or incinerate, Contents under pressure

• Do not store at temperature above 120⁰F

Stop use and ask a doctor if rash occurs.

PURPOSE

Avobenzone 3.0% ……………………………………………………………………………… Sunscreen

Homosalate 15.0% ……………………………………………………………………………. Sunscreen

Octisalate 5.0% …………………………………………………………………………………. Sunscreen

Octocrylene 10.0% ……………………………………………………………………………. Sunscreen

Stop use and ask a doctor if rash occurs.

Keep out of reach of children. If swallowed, get medical help or contact a Poison Control Center right away.

Inactive Ingredients

Acrylates/Octylacrylamide Copolymer

Alcohol Denat

Aloe Vera Oil Extract

Caprylic/Capric Triglyceride

Diethylhexyl Syringylidenemalonate

Glycerin

Tocopheryl Acetate

Retinyl Palmitate

WHEN USING

• keep out of eyes. Rinse with water to remove.

• Keep away from face to avoid breathing it.

• Do not puncture or incinerate, Contents under pressure

• Do not store at temperature above 120⁰F

Stop use and ask a doctor if rash occurs.

Warnings

For External use only.

INDICATIONS AND USAGE

For external use only

See Direction section for Dosage & Administration